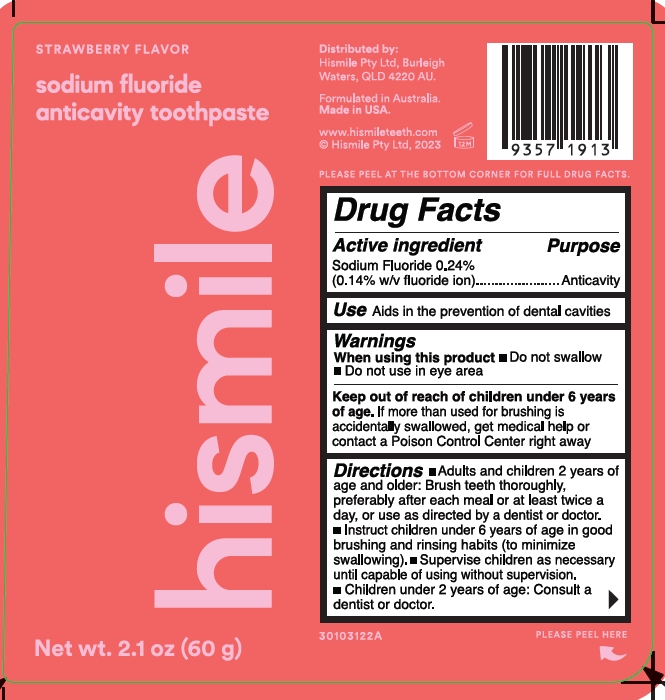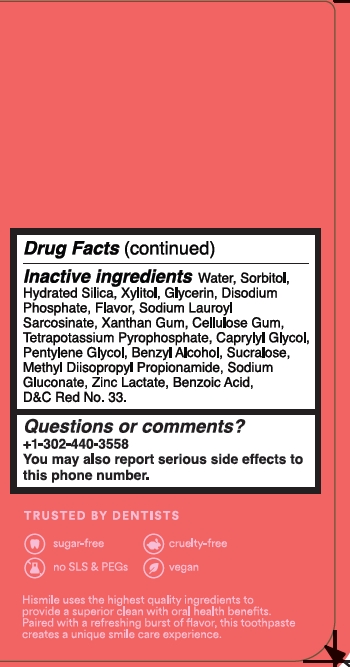 DRUG LABEL: Hismile
NDC: 83013-318 | Form: GEL
Manufacturer: Hismile Pty Ltd
Category: otc | Type: HUMAN OTC DRUG LABEL
Date: 20260115

ACTIVE INGREDIENTS: SODIUM FLUORIDE 2.4 mg/1 g
INACTIVE INGREDIENTS: D&C RED NO. 33; WATER; SODIUM LAUROYL SARCOSINATE; HYDRATED SILICA; GLYCERIN; CARBOXYMETHYLCELLULOSE SODIUM, UNSPECIFIED FORM; CAPRYLYL GLYCOL; PENTYLENE GLYCOL; METHYL DIISOPROPYL PROPIONAMIDE; SODIUM PHOSPHATE, DIBASIC, ANHYDROUS; SORBITOL; ZINC LACTATE; XANTHAN GUM; BENZYL ALCOHOL; BENZOIC ACID; SUCRALOSE; XYLITOL; POTASSIUM PYROPHOSPHATE; SODIUM GLUCONATE

Strawberry Flavor Sodium Fluoride Anticavity Toothpaste

Active ingredient

Sodium Fluoride 0.24% (0.14% w/v fluoride ion)

Purpose

Anticavity

Use

aids in the prevention of dental cavities

Warinings

Warnings

When using this product

- do not swallow
- do not use in eye area

Keep out of reach of children under 6 years of age. If more than used for brushing is accidentally swallowed, get medical help or contact a Poison Control Center right away.

Directions

- adults and children 2 years of ange and older：Brush teeth thoroughly preferably after each meal or at least twice a day, or use as directed by a dentist or doctor.
- instruct children under 6 years of age in good brushing and rinsing habits (to minimize swallowing).
- supervise children as necessary until capable of using without supervision.
- children under 2 years of age: Consult a dentist or doctor.

Inactive ingredients

Water, Sorbitol, Hydrated Silica, Xylitol, Glycerin, Disodium Phosphate, Flavor, Sodium Lauroyl Sarcosinate, Xanthan Gum, Cellulose Gum, Tetrapotassium Pyrophosphate, Caprylyl Glycol, Pentylene Glycol, Benzyl Alcohol, Sucralose, Methyl Diisopropyl Propionamide, Sodium Gluconate, Zinc Lactate, Benzoic Acid, D&C Red No. 33

Other information

Strawberry Flavor Sodium Fluoride Anticavity Toothpaste

Manufactured for:
Hismile Pty Ltd, 225 Burleigh
Connection Rd, Burleigh Waters,
Queensland, Australia 4220.

Formulated in Australia.
Made in USA.

www.hismileteeth.com
© Hismile Pty Ltd, 2022

TRUSTED BY DENTISTS

sugar-free
cruelty- free
no SLS & PEGs
vegan

Hismile uses the highest quality ingredients to provide a superior clean with oral health benefits. Paired with a refreshing burst of flavor, this toothpaste creates a unique smile care experience.